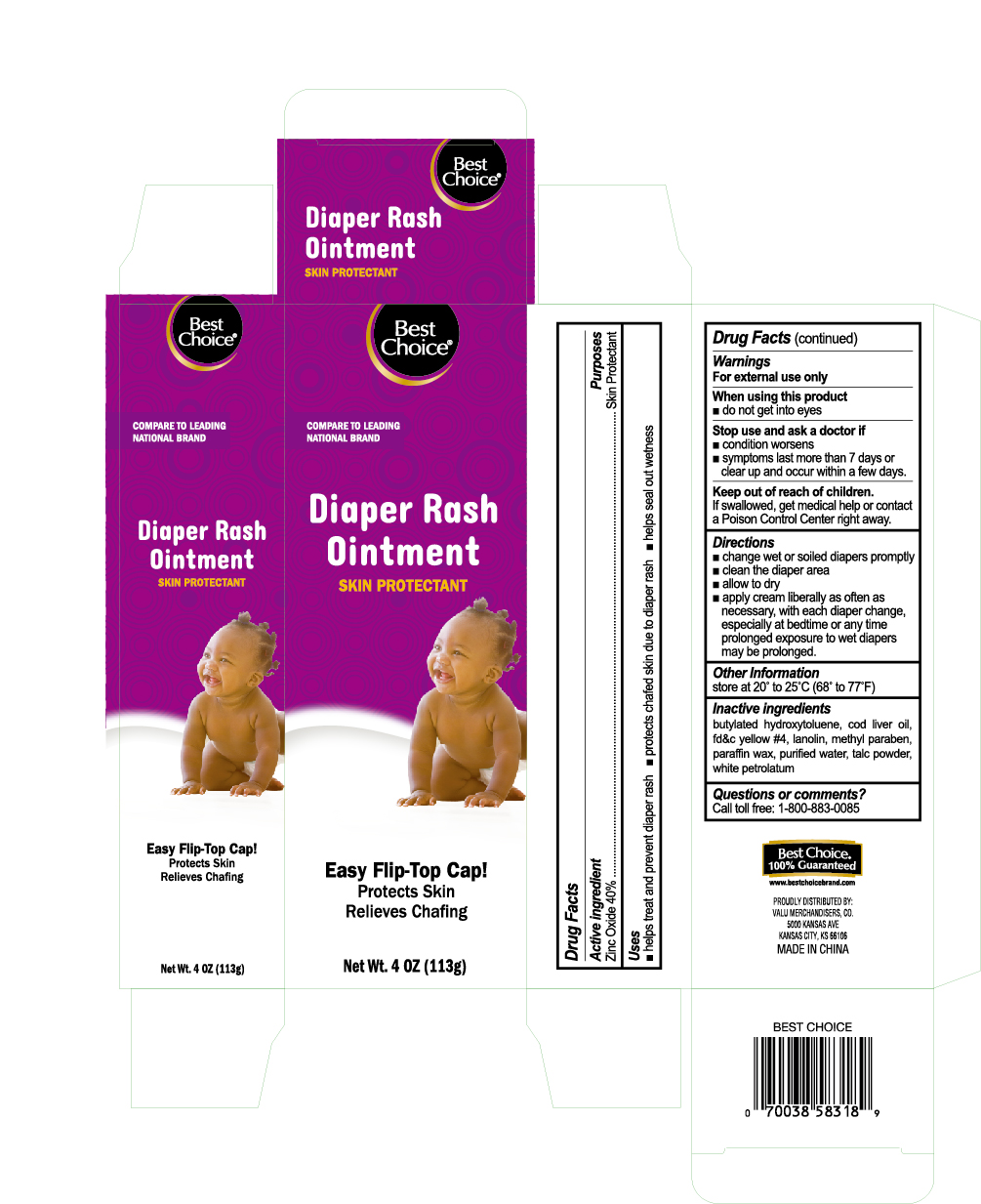 DRUG LABEL: Diaper Rash
NDC: 63941-318 | Form: CREAM
Manufacturer: Valu Merchandisers, Co.
Category: otc | Type: HUMAN OTC DRUG LABEL
Date: 20230208

ACTIVE INGREDIENTS: ZINC OXIDE 400 mg/1 g
INACTIVE INGREDIENTS: BUTYLATED HYDROXYTOLUENE; COD LIVER OIL; LANOLIN; METHYLPARABEN; PETROLATUM; TALC; WATER; PARAFFIN

Best Choice Diaper Rash Cream

Active ingredient

Zinc Oxide 40%

Purpose

Skin Protectant

Uses

- helps treat and prevent diaper rash
- protects chafed skin due to diaper rash
- helps seal out wetness

Warnings

For external and/or intrarectal use only

When using this product

- do not get into eyes

Stop use and ask a doctor if

- condition worsens
- symptoms last more than 7 days or clear up and occur within a few days

Keep out of reach of children.

If swallowed, get medical help or contact a Poison Control Center right away.

Directions

- change wet and soiled diapers promptly
- clean the diaper area
- allow to dry
- apply cream liberally as often as necessary, with each diaper change, especially at bedtime or anytime exposure to wet diapers may be prolonged

Other information

store at 20 to 25C (68 to 77F)

Inactive ingredients

butylated hydroxytoluene, cod liver oil, fd&c yellow #4, lanolin, methyl paraben, paraffin wax, purified water, talc powder, white petrolatum

Questions or comments?

Call toll free: 1-800-883-0085

Package label

Diaper Rash Cream